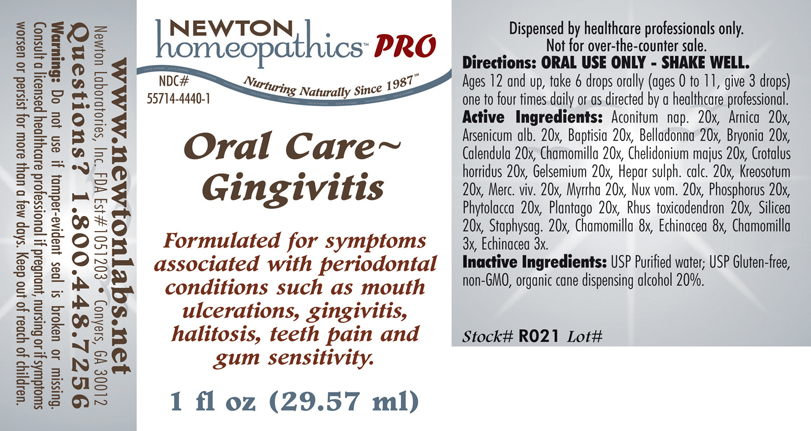 DRUG LABEL: Oral Care - Gingivitis 
NDC: 55714-4440 | Form: LIQUID
Manufacturer: Newton Laboratories, Inc.
Category: homeopathic | Type: HUMAN PRESCRIPTION DRUG LABEL
Date: 20110601

ACTIVE INGREDIENTS: Aconitum Napellus 20 [hp_X]/1 mL; Arnica Montana 20 [hp_X]/1 mL; Arsenic Trioxide 20 [hp_X]/1 mL; Baptisia Tinctoria Root 20 [hp_X]/1 mL; Atropa Belladonna 20 [hp_X]/1 mL; Bryonia Alba Root 20 [hp_X]/1 mL; Calendula Officinalis Flowering Top 20 [hp_X]/1 mL; Matricaria Recutita 20 [hp_X]/1 mL; Chelidonium Majus 20 [hp_X]/1 mL; Crotalus Horridus Horridus Venom 20 [hp_X]/1 mL; Gelsemium Sempervirens Root 20 [hp_X]/1 mL; Calcium Sulfide 20 [hp_X]/1 mL; Wood Creosote 20 [hp_X]/1 mL; Mercury 20 [hp_X]/1 mL; Myrrh 20 [hp_X]/1 mL; Strychnos Nux-vomica Seed 20 [hp_X]/1 mL; Phosphorus 20 [hp_X]/1 mL; Plantago Major 20 [hp_X]/1 mL; Toxicodendron Pubescens Leaf 20 [hp_X]/1 mL; Silicon Dioxide 20 [hp_X]/1 mL; Delphinium Staphisagria Seed 20 [hp_X]/1 mL; Echinacea, Unspecified 8 [hp_X]/1 mL
INACTIVE INGREDIENTS: Alcohol

Oral Care - Gingivitis

INDICATIONS & USAGE SECTION

Oral Care - Gingivitis Formulated for symptoms associated with periodontal conditions such as mouth ulcerations, gingivitis, halitosis, teeth pain and gum sensitivity.

DOSAGE & ADMINISTRATION SECTION

Directions: ORAL USE ONLY - SHAKE WELL. Ages 12 and up, take 6 drops orally (ages 0 to 11, give 3 drops) one to four times daily or as directed by a healthcare professional.

ACTIVE INGREDIENT SECTION

Aconitum nap. 20x, Arnica 20x, Arsenicum alb. 20x, Baptisia 20x, Belladonna 20x, Bryonia 20x, Calendula 20x, Chamomilla 20x, Chelidonium majus 20x, Crotalus horridus 20x, Gelsemium 20x, Hepar sulph. calc. 20x, Kreosotum 20x, Merc. viv. 20x, Myrrha 20x, Nux vom. 20x, Phosphorus 20x, Phytolacca 20x, Plantago 20x, Rhus toxicodendron 20x, Silicea 20x, Staphysag. 20x, Chamomilla 8x, Echinacea 8x, Chamomilla 3x, Echinacea 3x.

PURPOSE SECTION

Formulated for symptoms associated with periodontal conditions such as mouth ulcerations, gingivitis, halitosis, teeth pain and gum sensitivity.

INACTIVE INGREDIENT SECTION

Inactive Ingredients: USP Purified Water; USP Gluten-free, non-GMO, organic cane dispensing alcohol 20%.

QUESTIONS? SECTION

www.newtonlabs.net Newton Laboratories, Inc. FDA Est # 1051203 - Conyers, GA 30012
Questions? 1.800.448.7256

WARNINGS SECTION

Warning: Do not use if tamper - evident seal is broken or missing. Consult a licensed healthcare professional if pregnant, nursing or if symptoms worsen or persist for more than a few days. Keep out of reach of children.

PREGNANCY OR BREAST FEEDING SECTION

Consult a licensed healthcare professional if pregnant, nursing or if symptoms worsen or persist for more than a few days

KEEP OUT OF REACH OF CHILDREN SECTION

Keep out of reach of children